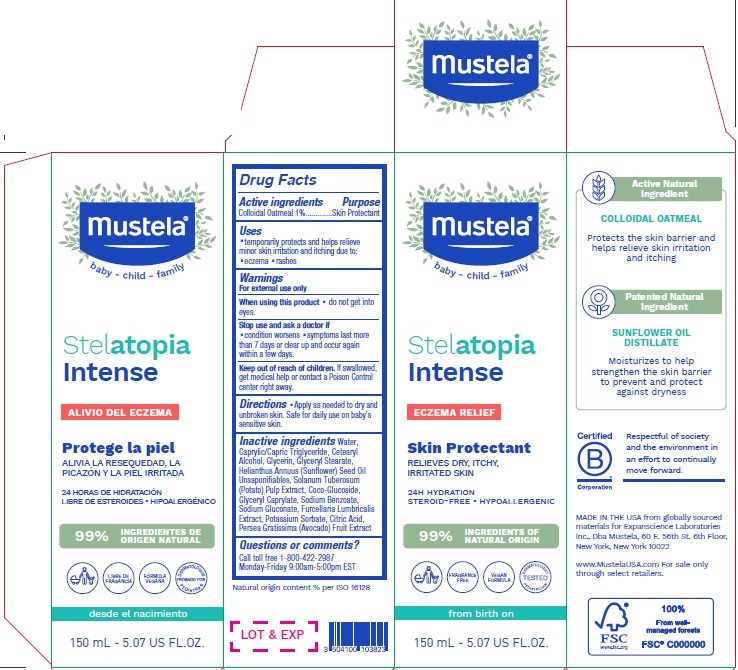 DRUG LABEL: Mustela Stelatopia Intense Eczema Relief Skin Protectant
NDC: 64768-7024 | Form: LOTION
Manufacturer: Expanscience Laboratories d/b/a Mustela
Category: otc | Type: HUMAN OTC DRUG LABEL
Date: 20241202

ACTIVE INGREDIENTS: OATMEAL 10 mg/1 mL
INACTIVE INGREDIENTS: POTATO PULP; SODIUM BENZOATE; FURCELLERAN; GLYCERYL CAPRYLATE; AVOCADO; GLYCERIN; CETOSTEARYL ALCOHOL; COCO GLUCOSIDE; SODIUM GLUCONATE; MEDIUM-CHAIN TRIGLYCERIDES; GLYCERYL MONOSTEARATE; CITRIC ACID MONOHYDRATE; WATER; POTASSIUM SORBATE

Mustela Stelatopia Intense Eczema Relief Skin Protectant

Active ingredients

Colloidal Oatmeal 1%

Purpose

Skin Protectant

Uses

- temporarily protects and helps relieve minor skin irritation and itching due to
- eczema
- rashes

Warnings

For external use only

When using this product

do not get into eyes.

Stop use and ask a doctor if

- condition worsens
- symptoms last more than 7 days or clear up and occur again within a few days.

Keep out of reach of children.

If swallowed, get medical help or contact a Poison Control center right away.

Directions

- Apply as needed to dry and unbroken skin. Safe for daily use on baby's sensitive skin.

Inactive ingredients

Water, Caprylic/Capric Triglyceride, Cetearyl Alcohol, Glycerin, Glyceryl Stearate, Helianthus Annuus (Sunfower) Seed Oil Unsaponifables, Solanum Tuberosum (Potato) Pulp Extract, Coco-Glucoside, Glyceryl Caprylate, Sodium Benzoate, Sodium Gluconate, Furcellaria Lumbricalis Extract, Potassium Sorbate, Citric Acid, Persea Gratissima (Avocado) Fruit Extract

Questions or comments?

Call toll free 1-800-422-2987
Monday-Friday 9:00am-5:00pm EST

Company Information

MADE IN THE USA from globally sourced
materials for Expanscience Laboratories
Inc., Dba Mustela, 60 E. 56th St. 6th Floor,
New York, New York 10022